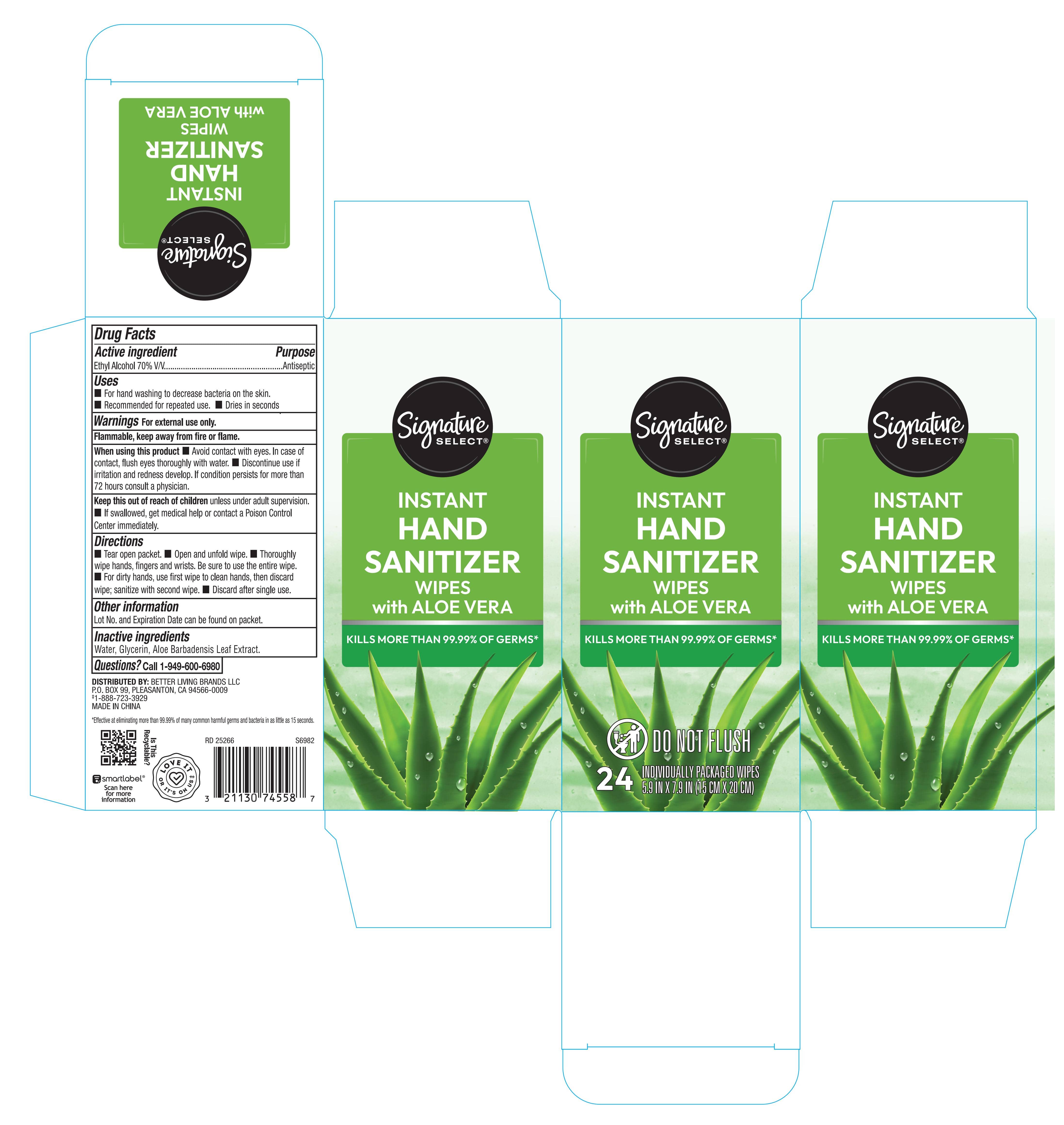 DRUG LABEL: Signature Select Instant Hand Sanitizer Wipes with Aloe Vera
NDC: 21130-068 | Form: SOLUTION
Manufacturer: Living Better Brands LLC
Category: otc | Type: HUMAN OTC DRUG LABEL
Date: 20260126

ACTIVE INGREDIENTS: ALCOHOL 70 mL/100 mL
INACTIVE INGREDIENTS: WATER; ALOE BARBADENSIS LEAF JUICE; GLYCERIN

21130-068 Alcohol wipe with Aloe

Active ingredient

Ethyl Alcohol 70% v/v

Purpose

Antiseptic

Uses

- For hand washing to decrease bacteria on the skin
- Recommended for repeated use
- Dries in seconds

Warnings

For external use only.

Flammable, keep away from fire or flame

When using this product

Avoid contact with eyes. In case of contact, flush eyes thoroughly with water

Discontinue use if irritation and redness develop. If condition persists for more than 72 hours, consult a physician.

KEEP OUT OF REACH OF CHILDREN

Keep out of reach of childrenunless under adult suoervision. If swallowed, get medical help or contact a Poison Control Center immediately.

Directions:

- Tear open packet
- Open and unfold wipe
- Thoroughly wipe hands, fingers, and wrists. Be sure to use the entire wipe.
- For dirty hands, use first wipe to clean hands, then discard wipe, sanitize with second wipe.
- Discard after single use

Other Information

Lot No and Expiration Date can be found on the packet

Inactive ingredients

Water, Glycerin, Aloe Barbadensis Leaf Extract